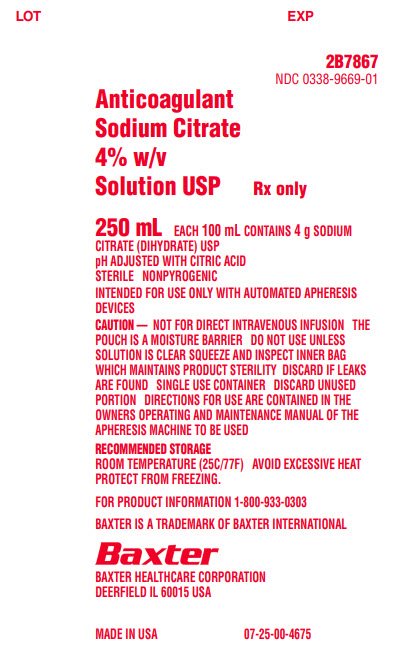 DRUG LABEL: ANTICOAGULANT SODIUM CITRATE
NDC: 0338-9669 | Form: SOLUTION
Manufacturer: Baxter Healthcare Corporation
Category: prescription | Type: HUMAN PRESCRIPTION DRUG LABEL
Date: 20240402

ACTIVE INGREDIENTS: TRISODIUM CITRATE DIHYDRATE 40 mg/1 mL
INACTIVE INGREDIENTS: WATER

ANTICOAGULANT SODIUM CITRATE 4% w/v SOLUTION USP

INDICATIONS AND USAGE

Anticoagulant Sodium Citrate 4% w/v Solution, USP is intended for use only with automated apheresis devices.

ADMINISTRATION

The pouch is a moisture barrier. Do not remove from pouch until ready to use. Do not use unless solution is clear and no leaks detected. Do not use unless port protector is in place.

DOSAGE FORMS AND STRENGTHS

Anticoagulant Sodium Citrate 4% w/v Solution, USP in the 250 mL single dose container is a sterile solution that contains 4g Sodium Citrate Dihydrate, USP per 100 mL, pH adjusted with citric acid.

PRECAUTIONS

Not for direct intravenous infusion.

HOW SUPPLIED

Anticoagulant Sodium Citrate 4% w/v Solution, USP is a clear solution supplied in sterile and nonpyrogenic PVC bags per carton.

Storage and Handling

Store at room temperature (25C/77F). Avoid excessive heat. Protect from freezing.

PACKAGE/LABEL PRINCIPAL DISPLAY PANEL

LOT

EXP

2B7867
NDC 0338-9669-01

Anticoagulant
Sodium Citrate
4% w/v
Solution USP

Rx only

250 mL EACH 100 mL CONTAINS 4 g SODIUM
CITRATE (DIHYDRATE) USP
pH ADJUSTED WITH CITRIC ACID
STERILE NONPYROGENIC
INTENDED FOR USE ONLY WITH AUTOMATED APHERESIS
DEVICES
CAUTION — NOT FOR DIRECT INTRAVENOUS INFUSION THE
POUCH IS A MOISTURE BARRIER DO NOT USE UNLESS
SOLUTION IS CLEAR SQUEEZE AND INSPECT INNER BAG
WHICH MAINTAINS PRODUCT STERILITY DISCARD IF LEAKS
ARE FOUND SINGLE USE CONTAINER DISCARD UNUSED
PORTION DIRECTIONS FOR USE ARE CONTAINED IN THE
OWNERS OPERATING AND MAINTENANCE MANUAL OF THE
APHERESIS MACHINE TO BE USED

RECOMMENDED STORAGE
ROOM TEMPERATURE (25C/77F) AVOID EXCESSIVE HEAT
PROTECT FROM FREEZING.

FOR PRODUCT INFORMATION 1-800-933-0303

BAXTER IS A TRADEMARK OF BAXTER INTERNATIONAL

Baxter Logo
BAXTER HEALTHCARE CORPORATION
DEERFIELD IL 60015 USA

MADE IN USA

07-25-00-4675